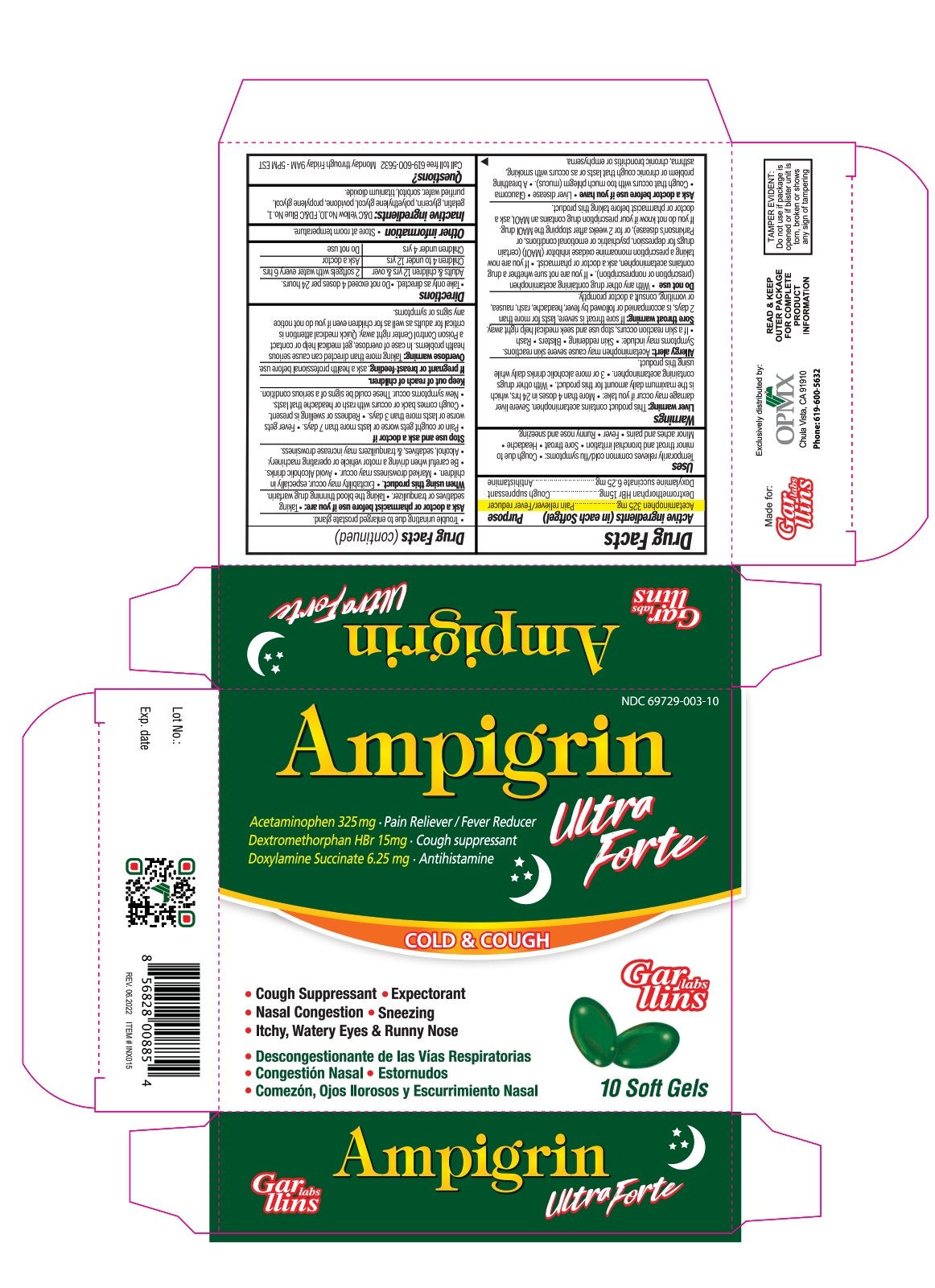 DRUG LABEL: Ampigrin Ultra Forte Night
NDC: 69729-003 | Form: CAPSULE, LIQUID FILLED
Manufacturer: OPMX LLC
Category: otc | Type: HUMAN OTC DRUG LABEL
Date: 20250717

ACTIVE INGREDIENTS: DEXTROMETHORPHAN HYDROBROMIDE 15 mg/1 1; DOXYLAMINE SUCCINATE 6.25 mg/1 1; ACETAMINOPHEN 325 mg/1 1
INACTIVE INGREDIENTS: FD&C BLUE NO. 1; GELATIN; GLYCERIN; POLYETHYLENE GLYCOL, UNSPECIFIED; POVIDONE; PROPYLENE GLYCOL; WATER; SORBITOL; D&C YELLOW NO. 10

Ampigrin Ultra Forte - Night

Drug Facts

ACTIVE INGREDIENT

Active ingredients (in each Softgels) | Purpose
Acetaminophen 325 mg | Pain reliever/fever reducer
Dextromethorphan HBr 15 mg | Cough suppressant
Doxylamine succinate 6.25 mg | Antihistamine

Uses

Temporarily relieves common cold/flu symptoms:

- Cough due to minor throat & bronchial irritation
- Sore throat
- Headache
- Minor aches & pains
- Fever
- Runny nose & sneezing

Warnings

Liver warning

This product contains acetaminophen. Severe liver damage may occur if you take

- more than 4 doses in 24 hrs, which is the maximum daily amount for this product
- with other drugs containing acetaminophen
- 3 or more alcoholic drinks daily while using this product

Allergy Alert

Acetaminophen may cause severe skin reactions. Symptoms may include:
• skin reddening • blisters • rash • If a skin reaction occurs, stop use and seek medical help right away

Sore throat warning

If sore throat is severe, lasts for more than 2 days, occurs with or is followed by fever, headache, rash, nausea, or vomiting, see a doctor promptly.

Do not use

- with any other drug containing acetaminophen (prescription or nonprescription). • If you are not sure whether a drug contains acetaminophen, ask a doctor or pharmacist.
- if you are now taking a prescription monoamine oxidase inhibitor (MAOI) (certain drugs for depression, psychiatric or emotional conditions, or Parkinson's disease), or for 2 weeks after stopping the MAOI drug. If you do not know if your prescription drug contains an MAOI, ask a doctor or pharmacist before taking this product.

Ask a doctor before use if you have

- liver disease
- glaucoma
- cough that occurs with too much phlegm (mucus)
- a breathing problem or chronic cough that lasts or as occurs with smoking, asthma, chronic bronchitis or emphysema
- trouble urinating due to enlarged prostate gland

When using this product

- Excitability may occur, especially in children
- Marked drowsiness may occur
- Avoid Alcoholic drinks
- Be careful when driving a motor vehicle or operating machinery
- Alcohol, sedatives, & tranquilizers may increase drowsiness

Stop use and ask a doctor if

- Pain or cough gets worse or lasts more than 7 days
- Fever gets worse or lasts more than 3 days
- Redness or swelling is present
- New symptoms occur
- Cough comes back or occurs with rash or headache that lasts. These could be signs of a serious condition.

If pregnant or breast-feeding,

ask a health professional before use.

Keep out of reach of children.

Overdose warning

In case of overdose, get medical help or contact a Poison Control Center right away. Quick medical attention is critical for adults & for children even if you do not notice any signs or symptoms.

Directions

- Take only as directed
- Do not exceed 4 doses per 24 hrs

Adults & children 12 yrs & over | 2 softgels with water every 6 hrs
Children 4 to under 12 yrs | Ask a doctor
Children under 4 yrs | Do not use

Other information

- Store at room temperature

Inactive ingredients

D&C Yellow No. 10, FD&C Blue No. 1, gelatin, glycerin, polyethylene glycol, povidone, propylene glycol, purified water, sorbitol special, titanium dioxide

Questions?

Call toll free 619-600-5632 Monday through Friday 9AM - 5PM EST

Made for:

RRX
Exclusively distributed by:

OPMX
Chula Vista, CA 91910

PRINCIPAL DISPLAY PANEL

NDC 69729-003-10

Ampigrin Ultra Forte

Acetaminophen 325 mg Pain Reliever/Fever Reducer

Dextromethorphan HBr 15 mg, Cough suppressant

Doxylamine Succinate 6.25 mg Antihistamine

COLD & COUGH

- Cough Suppressant
- Expectorant
- Nasal Congestion
- Sneezing
- Itchy, Watery Eyes & Runny Nose
- Descongestionante de las vías Respiratorias
- Congestión Nasal
- Estornudos
- Comezon, Ojos llorosos y Escurrimiento Nasal

10 Softgels